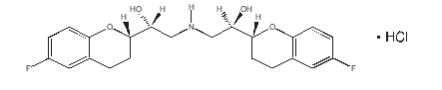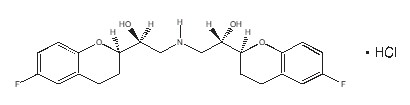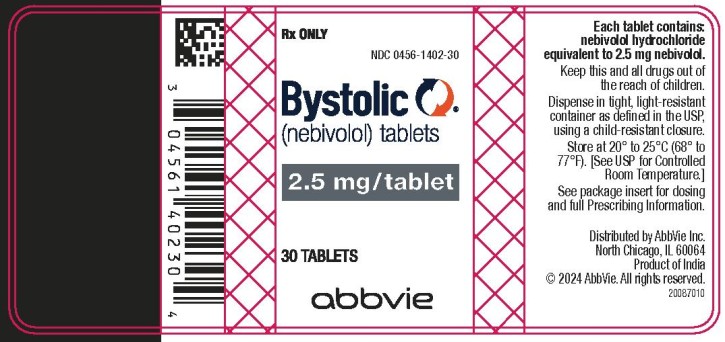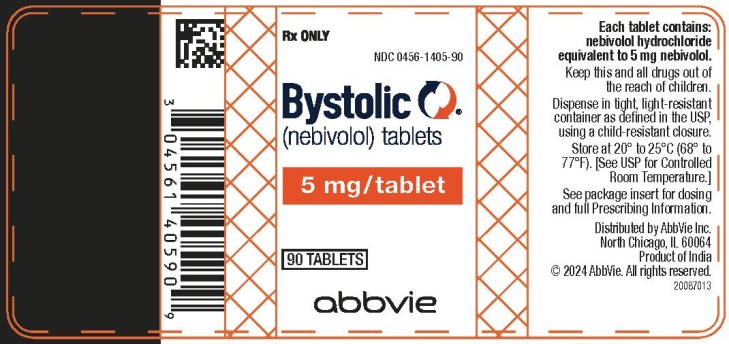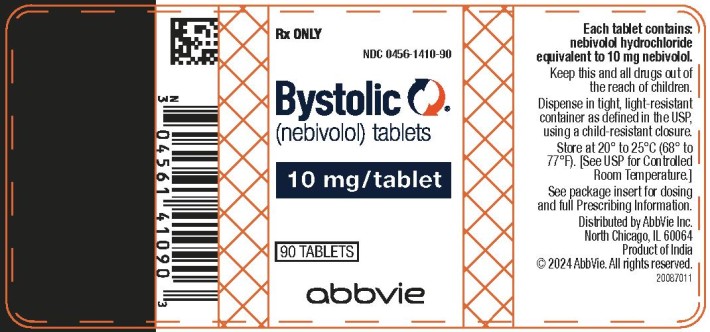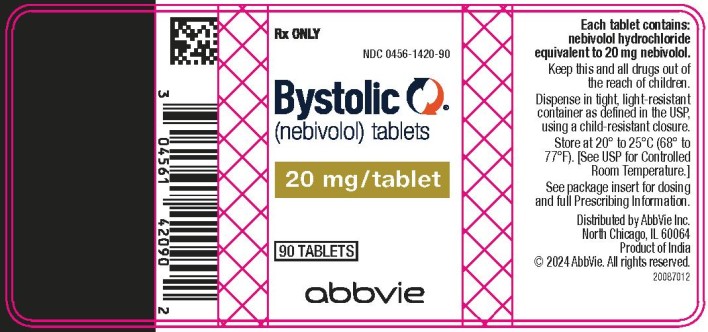 DRUG LABEL: Bystolic
NDC: 0456-1402 | Form: TABLET
Manufacturer: Allergan, Inc.
Category: prescription | Type: HUMAN PRESCRIPTION DRUG LABEL
Date: 20240801

ACTIVE INGREDIENTS: nebivolol hydrochloride 2.5 mg/1 1
INACTIVE INGREDIENTS: silicon dioxide; croscarmellose sodium; D&C RED NO. 27; FD&C BLUE NO. 2; FD&C YELLOW NO. 6; HYPROMELLOSE, UNSPECIFIED; lactose monohydrate; magnesium stearate; MICROCRYSTALLINE CELLULOSE; starch, corn; polysorbate 80; sodium lauryl sulfate

HIGHLIGHTS OF PRESCRIBING INFORMATION

These highlights do not include all the information needed to use BYSTOLIC safely and effectively. See full prescribing information for BYSTOLIC.
BYSTOLIC® (nebivolol) tablets, for oral use
Initial U.S. Approval: 2007

1. INDICATIONS AND USAGE

BYSTOLIC is a beta-adrenergic blocking agent indicated for the treatment of hypertension, to lower blood pressure. Lowering blood pressure reduces the risk of fatal and nonfatal cardiovascular events, primarily strokes and myocardial infarctions. (1.1)

2. DOSAGE AND ADMINISTRATION

Can be taken with and without food. Individualize to the needs of the patient and monitor during up-titration. (2)

- Hypertension: Most patients start at 5 mg once daily. Dose can be increased at 2-week intervals up to 40 mg. (2.1)

3. DOSAGE FORMS AND STRENGTHS

Tablets: 2.5, 5, 10, 20 mg (3)

4. CONTRAINDICATIONS

- Severe bradycardia (4)
- Heart block greater than first degree (4)
- Patients with cardiogenic shock (4)
- Decompensated cardiac failure (4)
- Sick sinus syndrome (unless a permanent pacemaker is in place) (4)
- Patients with severe hepatic impairment (Child-Pugh >B) (4)
- Hypersensitive to any component of this product (4)

5. WARNINGS AND PRECAUTIONS

- Acute exacerbation of coronary artery disease upon cessation of therapy: Do not abruptly discontinue. (5.1)
- Diabetes: May mask symptoms of hypoglycemia and alter glucose levels; monitor (5.5)

6. ADVERSE REACTIONS

Most common adverse reactions (6.1):

- Headache, fatigue

To report SUSPECTED ADVERSE REACTIONS, Contact AbbVie Inc. at 1-800-678-1605 or FDA at 1-800-FDA-1088 or www.fda.gov/medwatch.

7. DRUG INTERACTIONS

- CYP2D6 enzyme inhibitors may increase nebivolol levels. (7.1)
- Reserpine or clonidine may produce excessive reduction of sympathetic activity. (7.2)
- Both digitalis glycosides and β-blockers slow atrioventricular conduction and decrease heart rate. Concomitant use can increase the risk of bradycardia. (7.3)
- Verapamil- or diltiazem-type calcium channel blockers may cause excessive reductions in heart rate, blood pressure, and cardiac contractility. (7.4)

8. USE IN SPECIFIC POPULATIONS

- Lactation: Breastfeeding is not recommended. (8.2)

FULL PRESCRIBING INFORMATION

1. INDICATIONS AND USAGE

1.1 Hypertension

BYSTOLIC is indicated for the treatment of hypertension, to lower blood pressure [see Clinical Studies (14.1)]. BYSTOLIC may be used alone or in combination with other antihypertensive agents [see Drug Interactions (7)].

Lowering blood pressure reduces the risk of fatal and nonfatal cardiovascular events, primarily strokes and myocardial infarctions. These benefits have been seen in controlled trials of antihypertensive drugs from a wide variety of pharmacologic classes, including the class to which this drug principally belongs. There are no controlled trials demonstrating risk reduction with BYSTOLIC.

Control of high blood pressure should be part of comprehensive cardiovascular risk management, including, as appropriate, lipid control, diabetes management, antithrombotic therapy, smoking cessation, exercise, and limited sodium intake. Many patients will require more than one drug to achieve blood pressure goals. For specific advice on goals and management, see published guidelines, such as those of the National High Blood Pressure Education Program’s Joint National Committee on Prevention, Detection, Evaluation, and Treatment of High Blood Pressure (JNC).

Numerous antihypertensive drugs, from a variety of pharmacologic classes and with different mechanisms of action, have been shown in randomized controlled trials to reduce cardiovascular morbidity and mortality, and it can be concluded that it is blood pressure reduction, and not some other pharmacologic property of the drugs, that is largely responsible for those benefits. The largest and most consistent cardiovascular outcome benefit has been a reduction in the risk of stroke, but reductions in myocardial infarction and cardiovascular mortality also have been seen regularly.

Elevated systolic or diastolic pressure causes increased cardiovascular risk, and the absolute risk increase per mmHg is greater at higher blood pressures, so that even modest reductions of severe hypertension can provide substantial benefit. Relative risk reduction from blood pressure reduction is similar across populations with varying absolute risk, so the absolute benefit is greater in patients who are at higher risk independent of their hypertension (for example, patients with diabetes or hyperlipidemia), and such patients would be expected to benefit from more aggressive treatment to a lower blood pressure goal.

Some antihypertensive drugs have smaller blood pressure effects (as monotherapy) in black patients, and many antihypertensive drugs have additional approved indications and effects (e.g., on angina, heart failure, or diabetic kidney disease). These considerations may guide selection of therapy.

2. DOSAGE AND ADMINISTRATION

2.1 Hypertension

The dose of BYSTOLIC must be individualized to the needs of the patient. For most patients, the recommended starting dose is 5 mg once daily, with or without food, as monotherapy or in combination with other agents. For patients requiring further reduction in blood pressure, the dose can be increased at 2-week intervals up to 40 mg. A more frequent dosing regimen is unlikely to be beneficial.

Renal Impairment

In patients with severe renal impairment (ClCr less than 30 mL/min) the recommended initial dose is 2.5 mg once daily; titrate up slowly if needed. BYSTOLIC has not been studied in patients receiving dialysis [see Clinical Pharmacology (12.4)].

Hepatic Impairment

In patients with moderate hepatic impairment, the recommended initial dose is 2.5 mg once daily; titrate up slowly if needed. BYSTOLIC has not been studied in patients with severe hepatic impairment and therefore it is not recommended in that population [see Clinical Pharmacology (12.4)].

2.2 Subpopulations

Geriatric Patients

It is not necessary to adjust the dose in the elderly [see use in Specific Populations (8.5)].

CYP2D6 Polymorphism

No dose adjustments are necessary for patients who are CYP2D6 poor metabolizers. The clinical effect and safety profile observed in poor metabolizers were similar to those of extensive metabolizers [see Clinical Pharmacology (12.3)].

3. DOSAGE FORMS AND STRENGTHS

BYSTOLIC is available as tablets for oral administration containing nebivolol hydrochloride equivalent to 2.5, 5, 10, and 20 mg of nebivolol.

BYSTOLIC tablets are triangular-shaped, biconvex, unscored, differentiated by color and are engraved with “FL” on one side and the number of mg (2 ½, 5, 10, or 20) on the other side.

4. CONTRAINDICATIONS

BYSTOLIC is contraindicated in the following conditions:

- Severe bradycardia
- Heart block greater than first degree
- Patients with cardiogenic shock
- Decompensated cardiac failure
- Sick sinus syndrome (unless a permanent pacemaker is in place)
- Patients with severe hepatic impairment (Child-Pugh >B)
- Patients who are hypersensitive to any component of this product.

5. WARNINGS AND PRECAUTIONS

5.1 Abrupt Cessation of Therapy

Do not abruptly discontinue BYSTOLIC therapy in patients with coronary artery disease. Severe exacerbation of angina, myocardial infarction and ventricular arrhythmias have been reported in patients with coronary artery disease following the abrupt discontinuation of therapy with β-blockers. Myocardial infarction and ventricular arrhythmias may occur with or without preceding exacerbation of the angina pectoris. Caution patients without overt coronary artery disease against interruption or abrupt discontinuation of therapy. As with other β-blockers, when discontinuation of BYSTOLIC is planned, carefully observe and advise patients to minimize physical activity. Taper BYSTOLIC over 1 to 2 weeks when possible. If the angina worsens or acute coronary insufficiency develops, re-start BYSTOLIC promptly, at least temporarily.

5.2 Angina and Acute Myocardial Infarction

BYSTOLIC was not studied in patients with angina pectoris or who had a recent MI.

5.3 Bronchospastic Diseases

In general, patients with bronchospastic diseases should not receive β-blockers.

5.4 Anesthesia and Major Surgery

Because beta-blocker withdrawal has been associated with an increased risk of MI and chest pain, patients already on beta-blockers should generally continue treatment throughout the perioperative period. If BYSTOLIC is to be continued perioperatively, monitor patients closely when anesthetic agents which depress myocardial function, such as ether, cyclopropane, and trichloroethylene, are used. If β-blocking therapy is withdrawn prior to major surgery, the impaired ability of the heart to respond to reflex adrenergic stimuli may augment the risks of general anesthesia and surgical procedures.

The β-blocking effects of BYSTOLIC can be reversed by β-agonists, e.g., dobutamine or isoproterenol. However, such patients may be subject to protracted severe hypotension. Additionally, difficulty in restarting and maintaining the heartbeat has been reported with β-blockers.

5.5 Hypoglycemia

Beta-blockers may prevent early warning signs of hypoglycemia, such as tachycardia, and increase the risk for severe or prolonged hypoglycemia at anytime during treatment, especially in patients with diabetes mellitus or children and patients who are fasting (i.e., surgery, not eating regularly, or are vomiting). If severe hypoglycemia occurs, patients should be instructed to seek emergency treatment.

5.6 Thyrotoxicosis

β-blockers may mask clinical signs of hyperthyroidism, such as tachycardia. Abrupt withdrawal of β-blockers may be followed by an exacerbation of the symptoms of hyperthyroidism or may precipitate a thyroid storm.

5.7 Peripheral Vascular Disease

β-blockers can precipitate or aggravate symptoms of arterial insufficiency in patients with peripheral vascular disease.

5.8 Non-dihydropyridine Calcium Channel Blockers

Because of significant negative inotropic and chronotropic effects in patients treated with β-blockers and calcium channel blockers of the verapamil and diltiazem type, monitor the ECG and blood pressure in patients treated concomitantly with these agents.

5.9 Use with CYP2D6 Inhibitors

Nebivolol exposure increases with inhibition of CYP2D6 [see Drug Interactions (7)]. The dose of BYSTOLIC may need to be reduced.

5.10 Impaired Renal Function

Renal clearance of nebivolol is decreased in patients with severe renal impairment. BYSTOLIC has not been studied in patients receiving dialysis [see Clinical Pharmacology (12.4) and Dosage and Administration (2.1)].

5.11 Impaired Hepatic Function

Metabolism of nebivolol is decreased in patients with moderate hepatic impairment. BYSTOLIC has not been studied in patients with severe hepatic impairment [see Clinical Pharmacology (12.4) and Dosage and Administration (2.1)].

5.12 Risk of Anaphylactic Reactions

While taking β-blockers, patients with a history of severe anaphylactic reactions to a variety of allergens may be more reactive to repeated accidental, diagnostic, or therapeutic challenge. Such patients may be unresponsive to the usual doses of epinephrine used to treat allergic reactions.

5.13 Pheochromocytoma

In patients with known or suspected pheochromocytoma, initiate an α-blocker prior to the use of any β-blocker.

6. ADVERSE REACTIONS

6.1 Clinical Studies Experience

BYSTOLIC has been evaluated for safety in patients with hypertension and in patients with heart failure. The observed adverse reaction profile was consistent with the pharmacology of the drug and the health status of the patients in the clinical trials. Adverse reactions reported for each of these patient populations are provided below. Excluded are adverse reactions considered too general to be informative and those not reasonably associated with the use of the drug because they were associated with the condition being treated or are very common in the treated population.

The data described below reflect worldwide clinical trial exposure to BYSTOLIC in 6545 patients, including 5038 patients treated for hypertension and the remaining 1507 subjects treated for other cardiovascular diseases. Doses ranged from 0.5 mg to 40 mg. Patients received BYSTOLIC for up to 24 months, with over 1900 patients treated for at least 6 months, and approximately 1300 patients for more than one year.

HYPERTENSION: In placebo-controlled clinical trials comparing BYSTOLIC with placebo, discontinuation of therapy due to adverse reactions was reported in 2.8% of patients treated with nebivolol and 2.2% of patients given placebo. The most common adverse reactions that led to discontinuation of BYSTOLIC were headache (0.4%), nausea (0.2%) and bradycardia (0.2%).

Table 1 lists treatment-emergent adverse reactions that were reported in three 12-week, placebo-controlled monotherapy trials involving 1597 hypertensive patients treated with either 5 mg, 10 mg, or 20-40 mg of BYSTOLIC and 205 patients given placebo and for which the rate of occurrence was at least 1% of patients treated with nebivolol and greater than the rate for those treated with placebo in at least one dose group.

Table 1. Treatment-Emergent Adverse Reactions with an Incidence (over 6 weeks) ≥ 1% in BYSTOLIC-Treated Patients and at a Higher Frequency than Placebo-Treated Patients
System Organ Class – Preferred Term | Placebo (n = 205) (%) | Nebivolol 5 mg (n = 459) (%) | Nebivolol 10 mg (n = 461) (%) | Nebivolol 20-40 mg (n = 677) (%)
Cardiac Disorders
Bradycardia | 0 | 0 | 0 | 1
Gastrointestinal Disorders
Diarrhea | 2 | 2 | 2 | 3
Nausea | 0 | 1 | 3 | 2
General Disorders
Fatigue | 1 | 2 | 2 | 5
Chest pain | 0 | 0 | 1 | 1
Peripheral edema | 0 | 1 | 1 | 1
Nervous System Disorders
Headache | 6 | 9 | 6 | 7
Dizziness | 2 | 2 | 3 | 4
Psychiatric Disorders
Insomnia | 0 | 1 | 1 | 1
Respiratory Disorders
Dyspnea | 0 | 0 | 1 | 1
Skin and subcutaneous Tissue Disorders
Rash | 0 | 0 | 1 | 1

Listed below are other reported adverse reactions with an incidence of at least 1% in the more than 4300 patients treated with BYSTOLIC in controlled or open-label trials except for those already appearing in Table 1, terms too general to be informative, minor symptoms, or adverse reactions unlikely to be attributable to drug because they are common in the population. These adverse reactions were in most cases observed at a similar frequency in placebo-treated patients in the controlled studies.

Body as a Whole: asthenia.

Gastrointestinal System Disorders: abdominal pain

Metabolic and Nutritional Disorders: hypercholesterolemia

Nervous System Disorders: paraesthesia

6.2 Laboratory Abnormalities

In controlled monotherapy trials of hypertensive patients, BYSTOLIC was associated with an increase in BUN, uric acid, triglycerides and a decrease in HDL cholesterol and platelet count.

6.3 Postmarketing Experience

The following adverse reactions have been identified from spontaneous reports of BYSTOLIC received worldwide and have not been listed elsewhere. These adverse reactions have been chosen for inclusion due to a combination of seriousness, frequency of reporting or potential causal connection to BYSTOLIC. Adverse reactions common in the population have generally been omitted. Because these adverse reactions were reported voluntarily from a population of uncertain size, it is not possible to estimate their frequency or establish a causal relationship to BYSTOLIC exposure: abnormal hepatic function (including increased AST, ALT and bilirubin), acute pulmonary edema, acute renal failure, atrioventricular block (both second and third degree), bronchospasm, erectile dysfunction, hypersensitivity (including urticaria, allergic vasculitis and rare reports of angioedema), hypotension, myocardial infarction, pruritus, psoriasis, Raynaud’s phenomenon, peripheral ischemia/claudication, somnolence, syncope, thrombocytopenia, various rashes and skin disorders, vertigo, and vomiting.

7. DRUG INTERACTIONS

7.1 CYP2D6 Inhibitors

Use caution when BYSTOLIC is co-administered with CYP2D6 inhibitors (quinidine, propafenone, fluoxetine, paroxetine, etc.) [see Clinical Pharmacology (12.5)].

7.2 Hypotensive Agents

Do not use BYSTOLIC with other β-blockers. Closely monitor patients receiving catecholamine-depleting drugs, such as reserpine or guanethidine, because the added β-blocking action of BYSTOLIC may produce excessive reduction of sympathetic activity. In patients who are receiving BYSTOLIC and clonidine, discontinue BYSTOLIC for several days before the gradual tapering of clonidine.

7.3 Digitalis Glycosides

Both digitalis glycosides and β-blockers slow atrioventricular conduction and decrease heart rate. Concomitant use can increase the risk of bradycardia.

7.4 Calcium Channel Blockers

BYSTOLIC can exacerbate the effects of myocardial depressants or inhibitors of AV conduction, such as certain calcium antagonists (particularly of the phenylalkylamine [verapamil] and benzothiazepine [diltiazem] classes), or antiarrhythmic agents, such as disopyramide.

8. USE IN SPECIFIC POPULATIONS

8.1 Pregnancy

Risk Summary

Available data regarding use of BYSTOLIC in pregnant women are insufficient to determine whether there are drug-associated risks of adverse developmental outcomes. There are risks to the mother and fetus associated with poorly controlled hypertension in pregnancy. The use of beta blockers during the third trimester of pregnancy may increase the risk of hypotension, bradycardia, hypoglycemia, and respiratory depression in the neonate [see Clinical Considerations]. Oral administration of nebivolol to pregnant rats during organogenesis resulted in embryofetal and perinatal lethality at doses approximately equivalent to the maximum recommended human dose (MRHD).

The estimated background risk of major birth defects and miscarriage for the indicated population is unknown. In the U.S. general population, the estimated background risk of major birth defects and miscarriage in clinically recognized pregnancies is 2-4% and 15-20%, respectively.

Clinical Considerations

Disease-associated maternal and/or embryo/fetal risk

Hypertension in pregnancy increases the maternal risk for pre-eclampsia, gestational diabetes, premature delivery, and delivery complications (e.g., need for cesarean section, and post-partum hemorrhage). Hypertension increases the fetal risk for intrauterine growth restriction and intrauterine death. Pregnant women with hypertension should be carefully monitored and managed accordingly.

Fetal/Neonatal adverse reactions

Neonates of women with hypertension, who are treated with beta-blockers during the third trimester of pregnancy, may be at increased risk for hypotension, bradycardia, hypoglycemia, and respiratory depression. Observe newborns for symptoms of hypotension, bradycardia, hypoglycemia and respiratory depression and manage accordingly.

Data

Animal Data

Nebivolol was shown to increase embryo-fetal and perinatal lethality in rats at approximately 1.2 times the MRHD or 40 mg/day on a mg/m^2 basis. Decreased pup body weights occurred at 1.25 and 2.5 mg/kg in rats, when exposed during the perinatal period (late gestation, parturition and lactation). At 5 mg/kg and higher doses (1.2 times the MRHD), prolonged gestation, dystocia and reduced maternal care were produced with corresponding increases in late fetal deaths and stillbirths and decreased birth weight, live litter size and pup survival. These events occurred only when nebivolol was given during the perinatal period (late gestation, parturition and lactation). Insufficient numbers of pups survived at 5 mg/kg to evaluate the offspring for reproductive performance.

In studies in which pregnant rats were given nebivolol during organogenesis, reduced fetal body weights were observed at maternally toxic doses of 20 and 40 mg/kg/day (5 and 10 times the MRHD), and small reversible delays in sternal and thoracic ossification associated with the reduced fetal body weights and a small increase in resorption occurred at 40 mg/kg/day (10 times the MRHD).

No adverse effects on embryo-fetal viability, sex, weight or morphology were observed in studies in which nebivolol was given to pregnant rabbits at doses as high as 20 mg/kg/day (10 times the MRHD).

8.2 Lactation

Risk Summary

There is no information regarding the presence of nebivolol in human milk, the effects on the breastfed infant, or the effects on milk production. Nebivolol is present in rat milk [see Data]. Because of the potential for β-blockers to produce serious adverse reactions in nursing infants, especially bradycardia, BYSTOLIC is not recommended during nursing.

Data

In lactating rats, maximum milk levels of unchanged nebivolol were observed at 4 hours after single and repeat doses of 2.5 mg/kg/day. The daily dose (mg/kg body weight) ingested by a rat pup is 0.3% of the dam dose for unchanged nebivolol.

8.4 Pediatric Use

Safety and effectiveness in pediatric patients have not been established. Pediatric studies in ages newborn to 18 years old have not been conducted because of incomplete characterization of developmental toxicity and possible adverse effects on long-term fertility [see Nonclinical Toxicology (13.1)].

Juvenile Animal Toxicity Data

Daily oral doses of nebivolol to juvenile rats from post-natal day 14 to post-natal day 27 showed sudden unexplained death at exposures equal to those in human poor metabolizers given a single dose of 10 mg. No mortality was seen at half the adult human exposure.

In surviving rats, cardiomyopathy was seen at exposures greater than or equal to the human exposure. Male rat pups exposed to twice the human exposure showed decreases in total sperm count as well as decreases in the total and percentage of motile sperm.

8.5 Geriatric Use

Of the 2800 patients in the U.S. sponsored placebo-controlled clinical hypertension studies, 478 patients were 65 years of age or older. No overall differences in efficacy or in the incidence of adverse events were observed between older and younger patients.

8.6 Heart Failure

In a placebo-controlled trial of 2128 patients (1067 BYSTOLIC, 1061 placebo) over 70 years of age with chronic heart failure receiving a maximum dose of 10 mg per day for a median of 20 months, no worsening of heart failure was reported with nebivolol compared to placebo. However, if heart failure worsens consider discontinuation of BYSTOLIC.

10. OVERDOSAGE

In clinical trials and worldwide postmarketing experience there were reports of BYSTOLIC overdose. The most common signs and symptoms associated with BYSTOLIC overdosage are bradycardia and hypotension. Other important adverse reactions reported with BYSTOLIC overdose include cardiac failure, dizziness, hypoglycemia, fatigue and vomiting. Other adverse reactions associated with β-blocker overdose include bronchospasm and heart block.

The largest known ingestion of BYSTOLIC worldwide involved a patient who ingested up to 500 mg of BYSTOLIC along with several 100 mg tablets of acetylsalicylic acid in a suicide attempt. The patient experienced hyperhydrosis, pallor, depressed level of consciousness, hypokinesia, hypotension, sinus bradycardia, hypoglycemia, hypokalemia, respiratory failure and vomiting. The patient recovered.

Because of extensive drug binding to plasma proteins, hemodialysis is not expected to enhance nebivolol clearance.

If overdose occurs, provide general supportive and specific symptomatic treatment. Based on expected pharmacologic actions and recommendations for other β-blockers, consider the following general measures, including stopping BYSTOLIC, when clinically warranted:

Bradycardia: Administer IV atropine. If the response is inadequate, isoproterenol or another agent with positive chronotropic properties may be given cautiously. Under some circumstances, transthoracic or transvenous pacemaker placement may be necessary.

Hypotension: Administer IV fluids and vasopressors. Intravenous glucagon may be useful.

Heart Block (second or third degree): Monitor and treat with isoproterenol infusion. Under some circumstances, transthoracic or transvenous pacemaker placement may be necessary.

Congestive Heart Failure: Initiate therapy with digitalis glycoside and diuretics. In certain cases, consider the use of inotropic and vasodilating agents.

Bronchospasm: Administer bronchodilator therapy such as a short acting inhaled β2-agonist and/or aminophylline.

Hypoglycemia: Administer IV glucose. Repeated doses of IV glucose or possibly glucagon may be required.

Supportive measures should continue until clinical stability is achieved. The half-life of low doses of nebivolol is 12-19 hours.

Call the National Poison Control Center (800-222-1222) for the most current information on β-blocker overdose treatment.

11. DESCRIPTION

The chemical name for the active ingredient in BYSTOLIC (nebivolol) tablets is (1RS,1’RS)-1,1’-[(2RS,2’SR)-bis(6-fluoro-3,4-dihydro-2H-1-benzopyran-2-yl)]- 2,2’-iminodiethanol hydrochloride. Nebivolol is a racemate composed of d-Nebivolol and l-Nebivolol with the stereochemical designations of [SRRR]-nebivolol and [RSSS]-nebivolol, respectively. Nebivolol’s molecular formula is (C22H25F2NO4•HCl) with the following structural formula:

SRRR - or d-nebivolol hydrochloride

RSSS - or l-nebivolol hydrochloride

MW: 441.90 g/mol

Nebivolol hydrochloride is a white to almost white powder that is soluble in methanol, dimethylsulfoxide, and N,N-dimethylformamide, sparingly soluble in ethanol, propylene glycol, and polyethylene glycol, and very slightly soluble in hexane, dichloromethane, and methylbenzene.

BYSTOLIC as tablets for oral administration contains nebivolol hydrochloride equivalent to 2.5, 5, 10, and 20 mg of nebivolol base. In addition, BYSTOLIC contains the following inactive ingredients: colloidal silicon dioxide, croscarmellose sodium, D&C Red #27 Lake, FD&C Blue #2 Lake, FD&C Yellow #6 Lake, hypromellose, lactose monohydrate, magnesium stearate, microcrystalline cellulose, pregelatinized starch, polysorbate 80, and sodium lauryl sulfate.

12. CLINICAL PHARMACOLOGY

Nebivolol is a β-adrenergic receptor blocking agent. In extensive metabolizers (most of the population) and at doses less than or equal to 10 mg, nebivolol is preferentially β1 selective. In poor metabolizers and at higher doses, nebivolol inhibits both β1 - and β2 - adrenergic receptors. Nebivolol lacks intrinsic sympathomimetic and membrane stabilizing activity at therapeutically relevant concentrations. At clinically relevant doses, BYSTOLIC does not demonstrate α1-adrenergic receptor blockade activity. Various metabolites, including glucuronides, contribute to β-blocking activity.

12.1 Mechanism of Action

The mechanism of action of the antihypertensive response of BYSTOLIC has not been definitively established. Possible factors that may be involved include: (1) decreased heart rate, (2) decreased myocardial contractility, (3) diminution of tonic sympathetic outflow to the periphery from cerebral vasomotor centers, (4) suppression of renin activity and (5) vasodilation and decreased peripheral vascular resistance.

12.3 Pharmacokinetics

Nebivolol is metabolized by a number of routes, including glucuronidation and hydroxylation by CYP2D6. The active isomer (d-nebivolol) has an effective half-life of about 12 hours in CYP2D6 extensive metabolizers (most people), and 19 hours in poor metabolizers and exposure to d-nebivolol is substantially increased in poor metabolizers. This has less importance than usual, however, because the metabolites, including the hydroxyl metabolite and glucuronides (the predominant circulating metabolites), contribute to β-blocking activity.

Plasma levels of d–nebivolol increase in proportion to dose in EMs and PMs for doses up to 20mg. Exposure to l-nebivolol is higher than to d-nebivolol but l-nebivolol contributes little to the drug’s activity as d-nebivolol’s beta receptor affinity is > 1000-fold higher than l-nebivolol. For the same dose, PMs attain a 5-fold higher Cmax and 10-fold higher AUC of d-nebivolol than do EMs. d-Nebivolol accumulates about 1.5-fold with repeated once-daily dosing in EMs.

Absorption

Absorption of BYSTOLIC is similar to an oral solution. The absolute bioavailability has not been determined.

Mean peak plasma nebivolol concentrations occur approximately 1.5 to 4 hours post-dosing in EMs and PMs.

Food does not alter the pharmacokinetics of nebivolol. Under fed conditions, nebivolol glucuronides are slightly reduced. BYSTOLIC may be administered without regard to meals.

Distribution

The in vitro human plasma protein binding of nebivolol is approximately 98%, mostly to albumin, and is independent of nebivolol concentrations.

Metabolism

Nebivolol is predominantly metabolized via direct glucuronidation of parent and to a lesser extent via N-dealkylation and oxidation via cytochrome P450 2D6. Its stereospecific metabolites contribute to the pharmacologic activity [see Drug Interactions (7)].

Elimination

After a single oral administration of 14C-nebivolol, 38% of the dose was recovered in urine and 44% in feces for EMs and 67% in urine and 13% in feces for PMs. Essentially all nebivolol was excreted as multiple oxidative metabolites or their corresponding glucuronide conjugates.

12.4 Pharmacokinetics in Special Populations

Hepatic Disease

d-Nebivolol peak plasma concentration increased 3-fold, exposure (AUC) increased 10-fold, and the apparent clearance decreased by 86% in patients with moderate hepatic impairment (Child-Pugh Class B). No formal studies have been performed in patients with severe hepatic impairment and nebivolol should be contraindicated for these patients [see Dosage and Administration (2.1)].

Renal Disease

The apparent clearance of nebivolol was unchanged following a single 5 mg dose of BYSTOLIC in patients with mild renal impairment (ClCr 50 to 80 mL/min, n=7), and it was reduced negligibly in patients with moderate (ClCr 30 to 50 mL/min, n=9), but clearance was reduced by 53% in patients with severe renal impairment (ClCr <30 mL/min, n=5). No studies have been conducted in patients on dialysis [see Dosage and Administration (2.1)].

12.5 Drug-Drug Interactions

Drugs that inhibit CYP2D6 can be expected to increase plasma levels of nebivolol. When BYSTOLIC is co-administered with an inhibitor or an inducer of this enzyme, monitor patients closely and adjust the nebivolol dose according to blood pressure response. In vitro studies have demonstrated that at therapeutically relevant concentrations, d- and l-nebivolol do not inhibit any cytochrome P450 pathways.

Digoxin: Concomitant administration of BYSTOLIC (10 mg once daily) and digoxin (0.25 mg once daily) for 10 days in 14 healthy adult individuals resulted in no significant changes in the pharmacokinetics of digoxin or nebivolol [see Drug Interactions (7)].

Warfarin: Administration of BYSTOLIC (10 mg once daily for 10 days) led to no significant changes in the pharmacokinetics of nebivolol or R- or S-warfarin following a single 10 mg dose of warfarin. Similarly, nebivolol has no significant effects on the anticoagulant activity of warfarin, as assessed by Prothrombin time and INR profiles from 0 to 144 hours after a single 10 mg warfarin dose in 12 healthy adult volunteers.

Diuretics: No pharmacokinetic interactions were observed in healthy adults between nebivolol (10 mg daily for 10 days) and furosemide (40 mg single dose), hydrochlorothiazide (25 mg once daily for 10 days), or spironolactone (25 mg once daily for 10 days).

Ramipril: Concomitant administration of BYSTOLIC (10 mg once daily) and ramipril (5 mg once daily) for 10 days in 15 healthy adult volunteers produced no pharmacokinetic interactions.

Losartan: Concomitant administration of BYSTOLIC (10 mg single dose) and losartan (50 mg single dose) in 20 healthy adult volunteers did not result in pharmacokinetic interactions.

Fluoxetine: Fluoxetine, a CYP2D6 inhibitor, administered at 20 mg per day for 21 days prior to a single 10 mg dose of nebivolol to 10 healthy adults, led to an 8-fold increase in the AUC and 3-fold increase in Cmax for d-nebivolol [see Drug Interactions (7)].

Histamine-2 Receptor Antagonists: The pharmacokinetics of nebivolol (5 mg single dose) were not affected by the co-administration of ranitidine (150 mg twice daily). Cimetidine (400 mg twice daily) causes a 23% increase in the plasma levels of d-nebivolol.

Charcoal: The pharmacokinetics of nebivolol (10 mg single dose) were not affected by repeated co-administration (4, 8, 12, 16, 22, 28, 36, and 48 hours after nebivolol administration) of activated charcoal (Actidose®-Aqua).

Sildenafil: The co-administration of nebivolol and sildenafil decreased AUC and Cmax of sildenafil by 21 and 23% respectively. The effect on the Cmax and AUC for d-nebivolol was also small (< 20%). The effect on vital signs (e.g., pulse and blood pressure) was approximately the sum of the effects of sildenafil and nebivolol.

Other Concomitant Medications: Utilizing population pharmacokinetic analyses, derived from hypertensive patients, the following drugs were observed not to have an effect on the pharmacokinetics of nebivolol: acetaminophen, acetylsalicylic acid, atorvastatin, esomeprazole, ibuprofen, levothyroxine sodium, metformin, sildenafil, simvastatin, or tocopherol.

Protein Binding: No meaningful changes in the extent of in vitro binding of nebivolol to human plasma proteins were noted in the presence of high concentrations of diazepam, digoxin, diphenylhydantoin, enalapril, hydrochlorothiazide, imipramine, indomethacin, propranolol, sulfamethazine, tolbutamide, or warfarin. Additionally, nebivolol did not significantly alter the protein binding of the following drugs: diazepam, digoxin, diphenylhydantoin, hydrochlorothiazide, imipramine, or warfarin at their therapeutic concentrations.

13. NONCLINICAL TOXICOLOGY

13.1 Carcinogenesis, Mutagenesis, Impairment of Fertility

In a two-year study of nebivolol in mice, a statistically significant increase in the incidence of testicular Leydig cell hyperplasia and adenomas was observed at 40 mg/kg/day (5 times the maximally recommended human dose of 40 mg on a mg/m^2 basis). Similar findings were not reported in mice administered doses equal to approximately 0.3 or 1.2 times the maximum recommended human dose. No evidence of a tumorigenic effect was observed in a 24-month study in Wistar rats receiving doses of nebivolol 2.5, 10 and 40 mg/kg/day (equivalent to 0.6, 2.4, and 10 times the maximally recommended human dose). Co-administration of dihydrotestosterone reduced blood LH levels and prevented the Leydig cell hyperplasia, consistent with an indirect LH-mediated effect of nebivolol in mice and not thought to be clinically relevant in man.

A randomized, double-blind, placebo- and active-controlled, parallel-group study in healthy male volunteers was conducted to determine the effects of nebivolol on adrenal function, luteinizing hormone, and testosterone levels. This study demonstrated that 6 weeks of daily dosing with 10 mg of nebivolol had no significant effect on ACTH-stimulated mean serum cortisol AUC0-120 min, serum LH, or serum total testosterone.

Effects on spermatogenesis were seen in male rats and mice at ≥ 40 mg/kg/day (10 and 5 times the MRHD, respectively). For rats the effects on spermatogenesis were not reversed and may have worsened during a four week recovery period. The effects of nebivolol on sperm in mice, however, were partially reversible.

Mutagenesis: Nebivolol was not genotoxic when tested in a battery of assays (Ames, in vitro mouse lymphoma TK+/-, in vitro human peripheral lymphocyte chromosome aberration, in vivo Drosophila melanogaster sex-linked recessive lethal, and in vivo mouse bone marrow micronucleus tests).

14. CLINICAL STUDIES

14.1 Hypertension

The antihypertensive effectiveness of BYSTOLIC as monotherapy has been demonstrated in three randomized, double-blind, multi-center, placebo-controlled trials at doses ranging from 1.25 to 40 mg for 12 weeks (Studies 1, 2, and 3). A fourth placebo-controlled trial demonstrated additional antihypertensive effects of BYSTOLIC at doses ranging from 5 to 20 mg when administered concomitantly with up to two other antihypertensive agents (ACE inhibitors, angiotensin II receptor antagonists, and thiazide diuretics) in patients with inadequate blood pressure control.

The three monotherapy trials included a total of 2016 patients (1811 BYSTOLIC, 205 placebo) with mild to moderate hypertension who had baseline diastolic blood pressures (DBP) of 95 to 109 mmHg. Patients received either BYSTOLIC or placebo once daily for twelve weeks. Two of these monotherapy trials (Studies 1 and 2) studied 1716 patients in the general hypertensive population with a mean age of 54 years, 55% males, 26% non-Caucasians, 7% diabetics and 6% genotyped as PMs. The third monotherapy trial (Study 3) studied 300 Black patients with a mean age of 51 years, 45% males, 14% diabetics, and 3% as PMs.

Placebo-subtracted blood pressure reductions by dose for each study are presented in Table 2. Most studies showed increasing response to doses above 5 mg.

Table 2. Placebo-Subtracted Least-Square Mean Reductions in Trough Sitting Systolic/Diastolic Blood Pressure (SiSBP/SiDBP mmHg) by Dose in Studies with Once Daily BYSTOLIC
 | Nebivolol dose (mg)
 | 1.25 | 2.5 | 5.0 | 10 | 20 | 30-40
Study 1 | -6.6*/-5.1* | -8.5*/-5.6* | -8.1*/-5.5* | -9.2*/-6.3* | -8.7*/-6.9* | -11.7*/-8.3*
Study 2 |  |  | -3.8/-3.2* | -3.1/-3.9* | -6.3*/-4.5*
Study 3¶ |  | -1.5/-2.9 | -2.6/-4.9* | -6.0*/-6.1* | -7.2*/-6.1* | -6.8*/-5.5*
Study 4^ |  |  | -5.7*/-3.3* | -3.7*/-3.5* | -6.2*/-4.6*

* p<0.05 based on pair-wise comparison vs. placebo

¶ Study enrolled only African Americans.

^ Study on top of one or two other antihypertensive medications.

Study 4 enrolled 669 patients with a mean age of 54 years, 55% males, 54% Caucasians, 29% Blacks, 15% Hispanics, 1% Asians, 14% diabetics, and 5% PMs. BYSTOLIC, 5 mg to 20 mg, administered once daily concomitantly with stable doses of up to two other antihypertensive agents (ACE inhibitors, angiotensin II receptor antagonists, and thiazide diuretics) resulted in significant additional antihypertensive effects over placebo compared to baseline blood pressure.

Effectiveness was similar in subgroups analyzed by age and sex. Effectiveness was established in Blacks, but as monotherapy the magnitude of effect was somewhat less than in Caucasians.

The blood pressure lowering effect of BYSTOLIC was seen within two weeks of treatment and was maintained over the 24-hour dosing interval.

There are no trials of BYSTOLIC demonstrating reductions in cardiovascular risk in patients with hypertension, but at least one pharmacologically similar drug has demonstrated such benefits.

16. HOW SUPPLIED/STORAGE AND HANDLING

BYSTOLIC is available as tablets for oral administration containing nebivolol hydrochloride equivalent to 2.5, 5, 10, and 20 mg of nebivolol.

BYSTOLIC tablets are triangular-shaped, biconvex, unscored, differentiated by color and are engraved with “FL” on one side and the number of mg (2 ½, 5, 10, or 20) on the other side. BYSTOLIC tablets are supplied in the following strengths and package configurations:

BYSTOLIC
Tablet Strength | Package Configuration | NDC # | Tablet Color
2.5 mg | Bottle of 30 | 0456-1402-30 | Light Blue
 | Bottle of 90 | 0456-1402-90
 | Bottle of 100 | 0456-1402-01
 | 10 x 10 Unit Dose | 0456-1402-63
5 mg | Bottle of 30 | 0456-1405-30 | Beige
 | Bottle of 90 | 0456-1405-90
 | Bottle of 100 | 0456-1405-01
 | 10 x 10 Unit Dose | 0456-1405-63
10 mg | Bottle of 30 | 0456-1410-30 | Pinkish-Purple
 | Bottle of 90 | 0456-1410-90
 | Bottle of 100 | 0456-1410-01
 | 10 x 10 Unit Dose | 0456-1410-63
20 mg | Bottle of 30 | 0456-1420-30 | Light Blue
 | Bottle of 90 | 0456-1420-90
 | Bottle of 100 | 0456-1420-01
 | 10 x 10 Unit Dose | 0456-1420-63

Store at 20° to 25°C (68° to 77°F) [see USP for Controlled Room Temperature].

Dispense in a tight, light-resistant container as defined in the USP using a child-resistant closure.

17. PATIENT COUNSELING INFORMATION

See FDA-approved patient labeling (Patient Information).

- Patient Advice

Advise patients to take BYSTOLIC regularly and continuously, as directed. BYSTOLIC can be taken with or without food. If a dose is missed, take the next scheduled dose only (without doubling it). Do not interrupt or discontinue BYSTOLIC without consulting the physician.

Patients should know how they react to this medicine before they operate automobiles, use machinery, or engage in other tasks requiring alertness.

Advise patients to consult a physician if any difficulty in breathing occurs, or if they develop signs or symptoms of worsening congestive heart failure such as weight gain or increasing shortness of breath, or excessive bradycardia.

Caution patients subject to spontaneous hypoglycemia, or diabetic patients receiving insulin or oral hypoglycemic agents, that β-blockers may mask some of the manifestations of hypoglycemia, particularly tachycardia.

Inform patients or caregivers that there is a risk of hypoglycemia when BYSTOLIC is given to patients who are fasting or who are vomiting. Instruct patients or caregivers how to monitor for signs of hypoglycemia [see Warnings and Precautions (5.5)].

Distributed by:
AbbVie Inc.,
North Chicago
IL 60064, USA

Licensed from Mylan Laboratories, Inc.

Under license from Janssen Pharmaceutica N.V., Beerse, Belgium

Actidose®-Aqua is a registered trademark of Paddock Laboratories, LLC

BYSTOLIC and its design are trademarks of Allergan Sales, LLC, an AbbVie company.

© 2024 AbbVie. All rights reserved.
V3.1USPI1402

PATIENT INFORMATION

BYSTOLIC® (bi-STOL-ik)

(nebivolol) Tablets

Read the Patient Information that comes with BYSTOLIC before you start taking it and each time you get a refill. There may be new information. This information does not take the place of talking with your doctor about your medical condition or your treatment. If you have any questions about BYSTOLIC, ask your doctor or pharmacist.

WHAT IS BYSTOLIC?

BYSTOLIC is a kind of prescription medicine called a “beta-blocker”. BYSTOLIC treats:

- High blood pressure (hypertension)

BYSTOLIC can lower blood pressure when used by itself and with other medicines.

BYSTOLIC is not approved for children less than 18 years of age.

WHO SHOULD NOT TAKE BYSTOLIC?

Do not take BYSTOLIC if you:

- Have heart failure and are in the ICU or need medicines to keep up your blood circulation
- Have a slow heartbeat or your heart skips beats (irregular heartbeat)
- Have severe liver damage
- Are allergic to any ingredient in BYSTOLIC. The active ingredient is nebivolol. See the end of this leaflet for a list of ingredients.

WHAT SHOULD I TELL MY DOCTOR BEFORE TAKING BYSTOLIC?

Tell your doctor about all of your medical problems, including if you:

- Have asthma or other lung problems (such as bronchitis or emphysema)
- Have problems with blood flow in your feet and legs (peripheral vascular disease) BYSTOLIC can make symptoms of blood flow problems worse.
- Have diabetes and take medicine to control blood sugar
- Have thyroid problems
- Have liver or kidney problems
- Had allergic reactions to medications or have allergies
- Have a condition called pheochromocytoma
- Are pregnant or trying to become pregnant. It is not known if BYSTOLIC is safe for your unborn baby. Talk with your doctor about the best way to treat high blood pressure while you are pregnant.
- Are breastfeeding. It is not known if BYSTOLIC passes into your breast milk. You should not breastfeed while using BYSTOLIC.
- Are scheduled for surgery and will be given anesthetic agents

Tell your doctor about all the medicines you take. Include prescription and non-prescription medicines, vitamins, and herbal products. BYSTOLIC and certain other medicines can affect each other and cause serious side effects.

Keep a list of all the medicines you take. Show this list to your doctor and pharmacist before you start a new medicine.

HOW SHOULD I TAKE BYSTOLIC?

- Do not suddenly stop taking BYSTOLIC. You could have chest pain or a heart attack. If your doctor decides to stop BYSTOLIC, your doctor may slowly lower your dose over time before stopping it completely.
- Take BYSTOLIC every day exactly as your doctor tells you. Your doctor will tell you how much BYSTOLIC to take and how often. Your doctor may start with a low dose and raise it over time.
- Do not stop taking BYSTOLIC or change your dose without talking with your doctor.
- Take BYSTOLIC with or without food.
- If you miss a dose, take your dose as soon as you remember, unless it is close to the time to take your next dose. Do not take 2 doses at the same time. Take your next dose at the usual time.
- If you take too much BYSTOLIC, call your doctor or poison control center right away.

WHAT ARE POSSIBLE SIDE EFFECTS OF BYSTOLIC?

- Low blood pressure and feeling dizzy. If you feel dizzy, sit or lie down and tell your doctor right away.
- Tiredness
- Slow heartbeat
- Headache
- Leg swelling due to fluid retention (edema). Tell your doctor if you gain weight or have trouble breathing while taking BYSTOLIC.
- If you are diabetic or take medicine for high blood sugar or if you have a tendency to have low blood sugar, Bystolic can mask/cover some of the signs and symptoms that would tell you that your blood sugar may be low, like heart palpitations or rapid heart beating. Ask your doctor for other signs that may alert you when having low blood sugar.

Tell your doctor if you have any side effects that bother you or don’t go away.

HOW SHOULD I STORE BYSTOLIC?

- Store BYSTOLIC between 68° to 77°F (20° - 25°C).
- Safely throw away BYSTOLIC that is out of date or no longer needed.
- Keep BYSTOLIC and all medicines out of the reach of children.

GENERAL INFORMATION ABOUT BYSTOLIC

Doctors sometimes prescribe medicines for conditions not included in the patient information leaflets.

- Only use BYSTOLIC for the medical problem it was prescribed for.
- Do not give BYSTOLIC to other people, even if they have the same symptoms. It may harm them.

This leaflet summarizes the most important information about BYSTOLIC. For more information:

- Talk with your doctor.
- Ask your doctor or pharmacist for information about BYSTOLIC that is written for healthcare professionals.
- Visit www.BYSTOLIC.com on the web or call 1-800-678-1605.

WHAT IS IN BYSTOLIC?

Active Ingredient: Nebivolol

Inactive Ingredients: colloidal silicon dioxide, croscarmellose sodium, D&C Red #27 Lake, FD&C Blue #2 Lake, FD&C Yellow #6 Lake, hypromellose, lactose monohydrate, magnesium stearate, microcrystalline cellulose, pregelatinized starch, polysorbate 80, and sodium lauryl sulfate

WHAT IS HIGH BLOOD PRESSURE (HYPERTENSION)?

Blood pressure is the force in your blood vessels when your heart beats and when your heart rests. You have high blood pressure when the force is too great.

High blood pressure makes the heart work harder to pump blood through the body and causes damage to the blood vessels. BYSTOLIC tablets can help your blood vessels relax so your blood pressure is lower.

Medicines that lower your blood pressure lower your chance of having a stroke or heart attack.

Rev. 06 2023

Distributed by:
AbbVie Inc.,
North Chicago
IL 60064, USA

Licensed from Mylan Laboratories, Inc.

Under license from Janssen Pharmaceutica N.V., Beerse, Belgium

Actidose®-Aqua is a registered trademark of Paddock Laboratories, LLC

BYSTOLIC and its design are trademarks of Allergan Sales, LLC, an AbbVie company.

© 2024 AbbVie. All rights reserved.

V3.1PPI1402

PRINCIPAL DISPLAY PANEL

NDC 0456-1402-30
Rx ONLY
Bystolic®
(nebivolol) tablets
2.5 mg/tablet
30 TABLETS
abbvie

PRINCIPAL DISPLAY PANEL

NDC 0456-1405-90
Rx ONLY
Bystolic®
(nebivolol) tablets
5 mg/tablet
90 TABLETS
abbvie

PRINCIPAL DISPLAY PANEL

NDC 0456-1410-90
Rx ONLY
Bystolic®
(nebivolol) tablets
10 mg/tablet
90 TABLETS
abbvie

PRINCIPAL DISPLAY PANEL

NDC 0456-1420-90
Rx ONLY
Bystolic®
(nebivolol) tablets
20 mg/tablet
90 TABLETS
abbvie